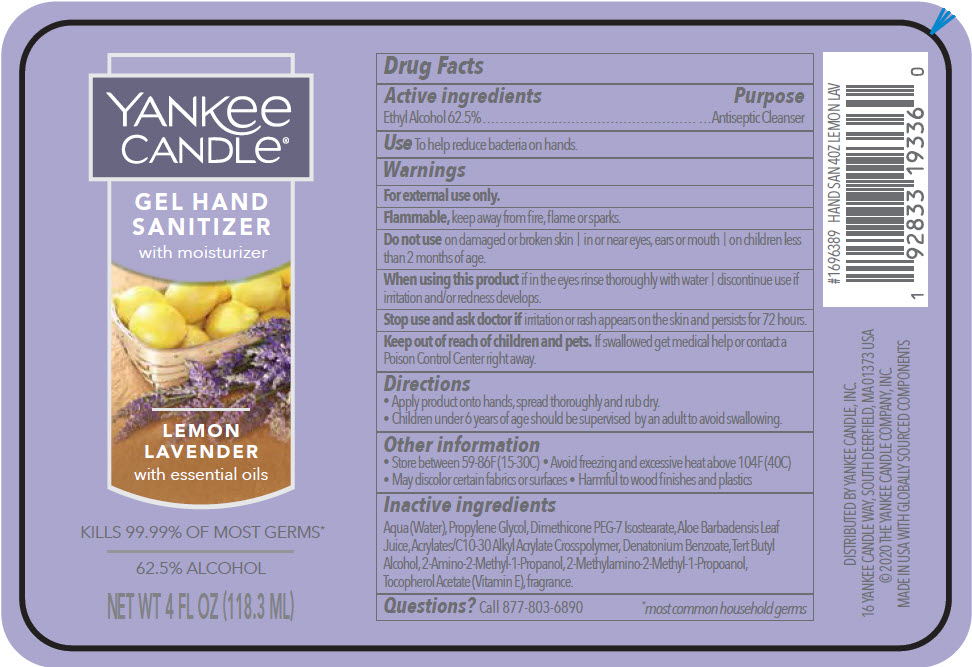 DRUG LABEL: YANKEE CANDLE HAND SANITIZER with moisturizer 
NDC: 80123-002 | Form: GEL
Manufacturer: THE YANKEE CANDLE COMPANY INC
Category: otc | Type: HUMAN OTC DRUG LABEL
Date: 20200831

ACTIVE INGREDIENTS: Alcohol 62.5 mL/100 mL
INACTIVE INGREDIENTS: WATER; ALOE VERA LEAF; CARBOMER INTERPOLYMER TYPE A (ALLYL SUCROSE CROSSLINKED); DENATONIUM BENZOATE; TERT-BUTYL ALCOHOL; AMINOMETHYLPROPANOL; PROPYLENE GLYCOL; DIMETHICONE PEG-7 ISOSTEARATE; .ALPHA.-TOCOPHEROL

YANKEE CANDLE® HAND SANITIZER with moisturizer
Lemon Lavender

Drug Facts

Active ingredients

Ethyl Alcohol 62.5%

Purpose

Antiseptic Cleanser

Use

To help reduce bacteria on hands.

Warnings

For external use only.

Flammable, keep away from fire, flame or sparks.

Do not use on damaged or broken skin | in or near eyes, ears or mouth | on children less than 2 months of age.

When using this product if in the eyes rinse thoroughly with water | discontinue use if irritation and/or redness develops.

Stop use and ask doctor if irritation or rash appears on the skin and persists for 72 hours.

Keep out of reach of children and pets. If swallowed get medical help or contact a Poison Control Center right away.

Directions

- Apply product onto hands, spread thoroughly and rub dry.
- Children under 6 years of age should be supervised by an adult to avoid swallowing.

Other information

- Store between 59-86F (15-30C)
- Avoid freezing and excessive heat above 104F (40C)
- May discolor certain fabrics or surfaces
- Harmful to wood finishes and plastics

Inactive ingredients

Aqua (Water), Propylene Glycol, Dimethicone PEG-7 Isostearate, Aloe Barbadensis Leaf Juice, Acrylates/C10-30 Alkyl Acrylate Crosspolymer, Denatonium Benzoate, Tert Butyl Alcohol, 2-Amino-2-Methyl-1-Propanol, 2-Methylamino-2-Methyl-1-Propoanol, Tocopherol Acetate (Vitamin E), fragrance.

Questions?

Call 877-803-6890

DISTRIBUTED BY YANKEE CANDLE, INC.
16 YANKEE CANDLE WAY, SOUTH DEERFIELD, MA 01373 USA

PRINCIPAL DISPLAY PANEL - 118.3 ML Bottle Label

YANKee
CANDLe®

GEL HAND
SANITIZER
with moisturizer

LEMON
LAVENDER
with essential oils

KILLS 99.99% OF MOST GERMS*

62.5% ALCOHOL

NET WT 4 FL OZ (118.3 ML)